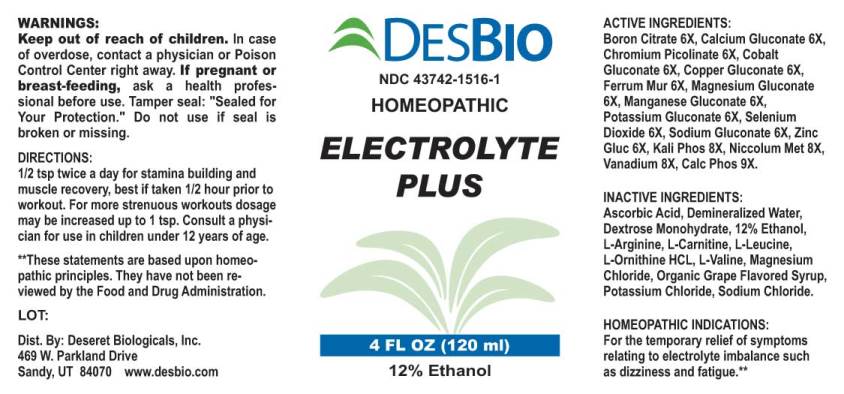 DRUG LABEL: Electrolyte Plus
NDC: 43742-1516 | Form: LIQUID
Manufacturer: Deseret Biologicals, Inc.
Category: homeopathic | Type: HUMAN OTC DRUG LABEL
Date: 20231011

ACTIVE INGREDIENTS: BORON CITRATE 6 [hp_X]/1 mL; CALCIUM GLUCONATE 6 [hp_X]/1 mL; CHROMIUM PICOLINATE 6 [hp_X]/1 mL; COBALTOUS GLUCONATE 6 [hp_X]/1 mL; COPPER GLUCONATE 6 [hp_X]/1 mL; FERRIC CHLORIDE HEXAHYDRATE 6 [hp_X]/1 mL; MAGNESIUM GLUCONATE 6 [hp_X]/1 mL; MANGANESE GLUCONATE 6 [hp_X]/1 mL; POTASSIUM GLUCONATE 6 [hp_X]/1 mL; SELENIUM DIOXIDE 6 [hp_X]/1 mL; SODIUM GLUCONATE 6 [hp_X]/1 mL; ZINC GLUCONATE 6 [hp_X]/1 mL; DIBASIC POTASSIUM PHOSPHATE 8 [hp_X]/1 mL; NICKEL 8 [hp_X]/1 mL; VANADIUM 8 [hp_X]/1 mL; TRIBASIC CALCIUM PHOSPHATE 9 [hp_X]/1 mL
INACTIVE INGREDIENTS: ASCORBIC ACID; DEXTROSE MONOHYDRATE; ALCOHOL; ARGININE; LEVOCARNITINE; LEUCINE; ORNITHINE; VALINE; MAGNESIUM CHLORIDE; GRAPE; POTASSIUM CHLORIDE; SODIUM CHLORIDE; WATER

Drug Facts:

ACTIVE INGREDIENTS:

Boron Citrate 6X, Calcium Gluconate 6X, Chromium Picolinate 6X, Cobalt Gluconate 6X, Copper Gluconate 6X, Ferrous Muriaticum 6X, Magnesium Gluconicum Dihydricum 6X, Manganese Gluconate 6X, Potassium Gluconate 6X, Selenium Dioxide 6X, Sodium Gluconate 6X, Zincum Gluconicum 6X, Kali Phosphoricum 8X, Niccolum Metallicum 8X, Vanadium Metallicum 8X, Calcarea Phosphorica 9X.

HOMEOPATHIC INDICATIONS:

For the temporary relief of symptoms relating to electrolyte imbalance such as dizziness and fatigue.**

**These statements are based upon traditional homeopathic principles. They have not been reviewed by the Food and Drug Administration.

WARNINGS:

Keep out of reach of children. In case of overdose, contact physician or Poison Control Center right away.

If pregnant or breast-feeding, seek advice of a health professional before use.

Tamper seal: "Sealed for Your Protection."

Do not use if seal is broken or missing.

Keep out of reach of children. In case of overdose, contact physician or Poison Control Center right away.

DIRECTIONS:

1/2 tsp twice a day for stamina building and muscle recovery, best if taken 1/2 hour prior to workout. For more strenuous workouts dosage may be increased up to 1 tsp. Consult a physician for use in children under 12 years of age.

HOMEOPATHIC INDICATIONS:

For the temporary relief of symptoms relating to electrolyte imbalance such as dizziness and fatigue.**

**These statements are based upon traditional homeopathic principles. They have not been reviewed by the Food and Drug Administration.

INACTIVE INGREDIENTS:

Ascorbic Acid, Demineralized Water, Dextrose Monohydrate, 12% Ethanol, L-Arginine, L-Carnitine, L-Leucine, L-Ornithine HCL, L-Valine, Magnesium Chloride, Organic Grape Flavored Syrup, Potassium Chloride, Sodium Chloride.

QUESTIONS:

Dist. by: Deseret Biologicals, Inc.

469 W. Parkland Drive

Sandy, UT 84070 www.desbio.com

PACKAGE LABEL DISPLAY:

DESBIO

NDC 43742-1516-1

HOMEOPATHIC

ELECTROLYTE
PLUS

4 FL OZ (120 ml)